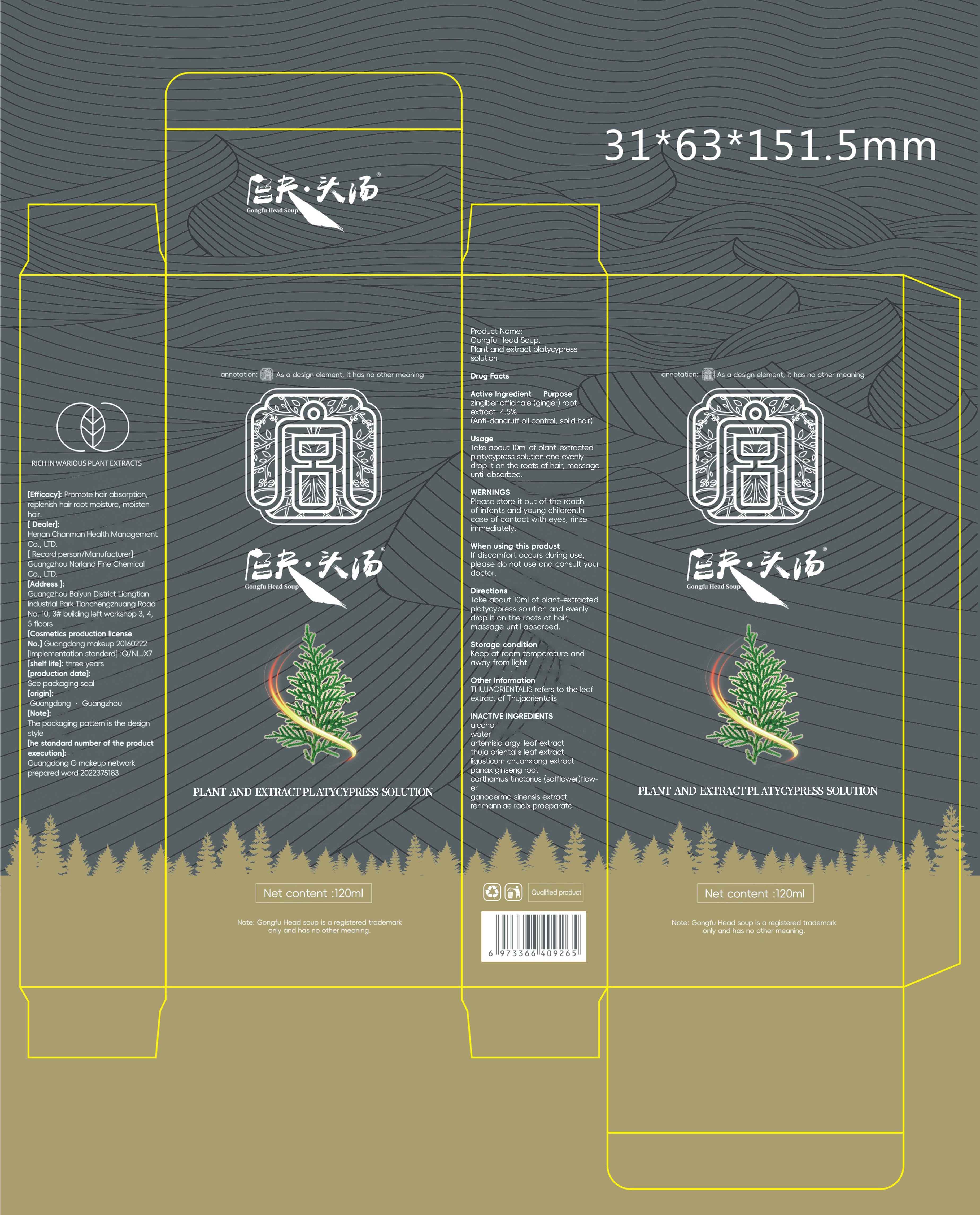 DRUG LABEL: Gongfu Head Soup Plant and extract platycypresssolution
NDC: 84286-008 | Form: LIQUID
Manufacturer: Henan Chanman Health Management Co., Ltd
Category: otc | Type: HUMAN OTC DRUG LABEL
Date: 20240507

ACTIVE INGREDIENTS: GINGER 4.5 g/100 mL
INACTIVE INGREDIENTS: WATER; ARTEMISIA ARGYI LEAF; PLATYCLADUS ORIENTALIS LEAF; ASIAN GINSENG; SAFFLOWER; GANODERMA JAPONICUM WHOLE; REHMANNIA GLUTINOSA ROOT; LIGUSTICUM SINENSE SUBSP. CHUANXIONG WHOLE

84286-008

Active Ingredient

zingiber officinale (ginger) root extract 4.5%

Purpose

Anti-dandruff oil control, solid hair

Use

Take about 10ml of plant-extractedplatycypress solution and evenlydrop it on the roots of hair, massageuntil absorbed.

Warnings

Please store it out of the reachof infants and young children.Incase of contact with eyes, rinseimmediately.

Do not use

If discomfort occurs during use，please do not use and consult your doctor.

When Using

If discomfort occurs during use，please do not use and consult your doctor.

Stop Use

If discomfort occurs during use，please do not use and consult your doctor.

Ask Doctor

If discomfort occurs during use，please do not use and consult your doctor.

Keep Oot Of Reach Of Children

Please store it out of the reachof infants and young children

Directions

Take about 10ml of plant-extractedplatycypress solution and evenlydrop it on the roots of hair, massage until absorbed.

Other information

THUJAORIENTALIS refers to the leafextract of Thujaorientalis

Inactive ingredients

Water
artemisia argyi leaf extract
thuja orientalis leaf extract
ligusticum chuanxiong extract
panax ginseng root
carthamus tinctorius (safflower)flower
ganoderma sinensis extract
rehmanniae radix praeparata